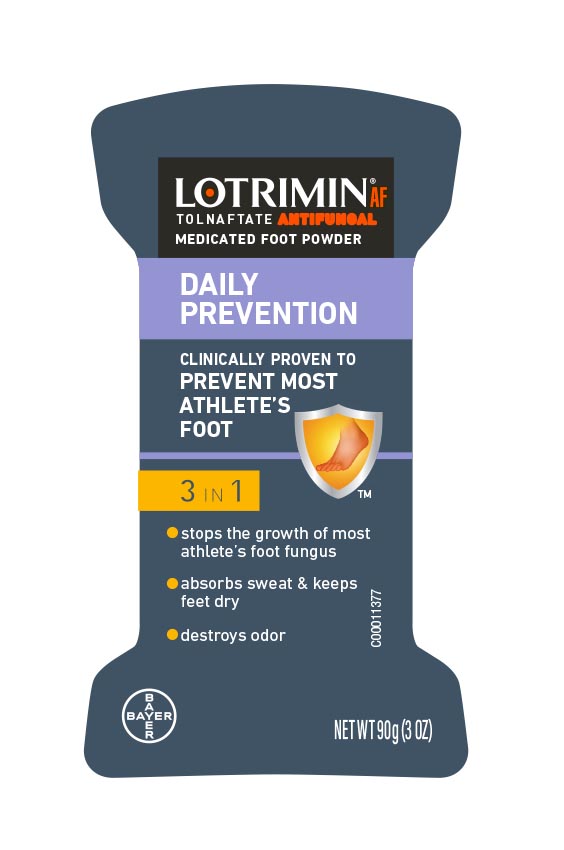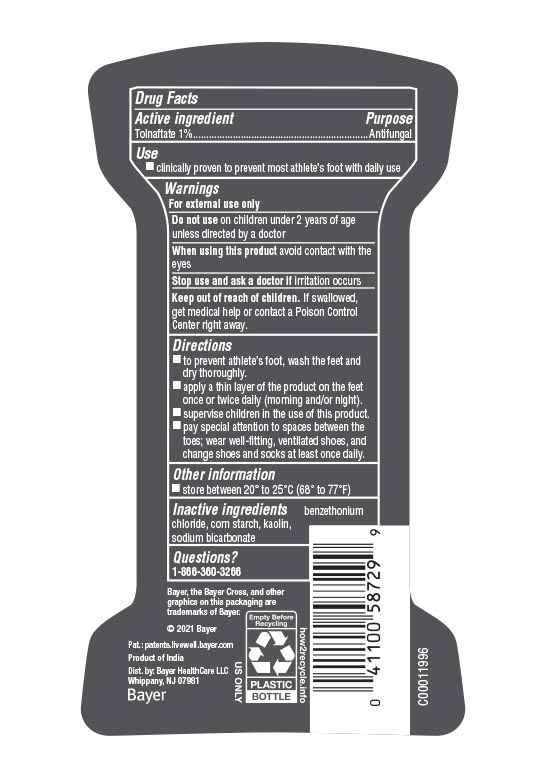 DRUG LABEL: Lotrimin Daily Prevention
NDC: 11523-0011 | Form: POWDER
Manufacturer: Bayer HealthCare LLC.
Category: otc | Type: HUMAN OTC DRUG LABEL
Date: 20260116

ACTIVE INGREDIENTS: TOLNAFTATE 10 mg/1 g
INACTIVE INGREDIENTS: KAOLIN; SODIUM BICARBONATE; STARCH, CORN; BENZETHONIUM CHLORIDE

Lotrimin Daily Prevention Powder UI 1612510

Drug Facts

Active ingredient

Tolnaftate 1%

Purpose

Antifungal

Use

• clinically proven to prevent most athlete' s foot with daily use

Warnings

For external use only

Do not use on children under 2 years of age unless directed by a doctor

When using this product avoid contact with the eyes

Stop use and ask a doctor if irritation occurs

Keep out of reach of children. If swallowed, get medical help or contact a Poison Control Center right away.

Directions

• to prevent athlete's foot, wash the feet and dry thoroughly.

• apply a thin layer of the product on the feet once or twice daily (morning and/or night).

• supervise children in the use of this product.

• pay special attention to spaces between the toes; wear well-fitting ventilated shoes and socks at least

once daily.

Other information

store between 20º to 25ºC (68º– 77ºF)

Inactive ingredients

benzethonium chloride;corn starch, kaolin;sodium bicarbonate

Questions

Questions? 1-866-360-3266

Package Display 3 oz. label

LOTRIMIN® AF

TOLNAFTATE ANTIFUNGAL

medicated foot powder

DAILY

PREVENTION

clinically proven to

prevent most

athlete's foot

- stops the growth of most athlete's foot fungus
- absorbs sweat & keeps feet dry
- destroys odor

NET WT 90g (3 OZ)